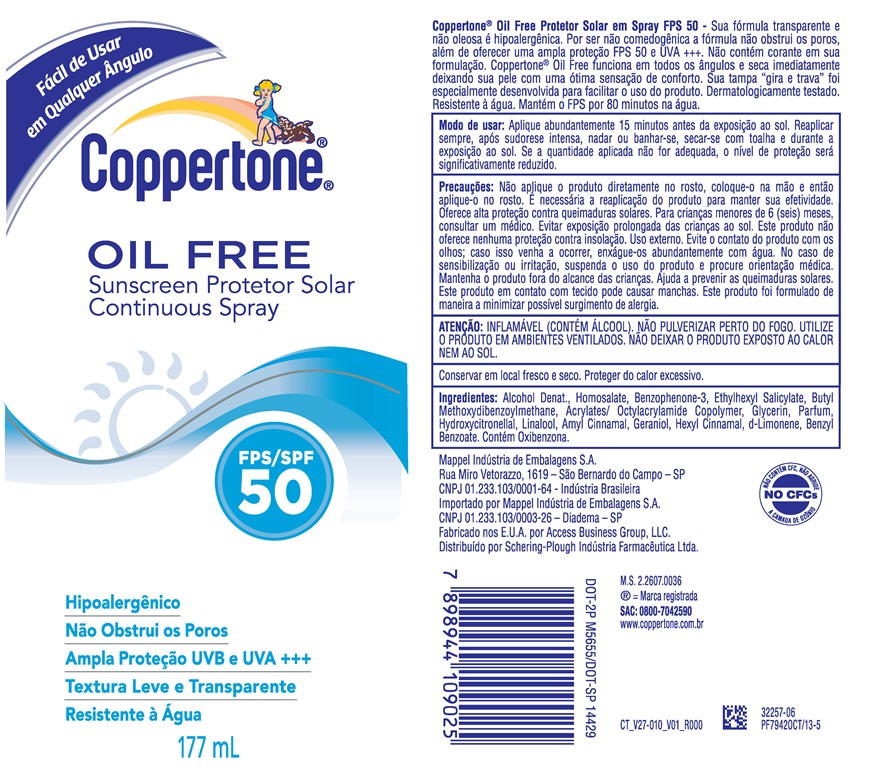 DRUG LABEL: coppertone

NDC: 11523-7380 | Form: SPRAY
Manufacturer: Bayer HealthCare LLC.
Category: otc | Type: HUMAN OTC DRUG LABEL
Date: 20200120

ACTIVE INGREDIENTS: HOMOSALATE 118.2 mg/1 mL; OCTISALATE 39.43 mg/1 mL; OXYBENZONE 52 mg/1 mL; AVOBENZONE 26 mg/1 mL
INACTIVE INGREDIENTS: ALCOHOL; GLYCERIN

Coppertone Sunscreen Oil Free Continuous Spray SPF 50

ACTIVE INGREDIENT

Each 1mL contains:

Avobenzone 26 mg

Homosalate 118.2 mg

Octisalate 39.43mg

Oxybenzone 52mg